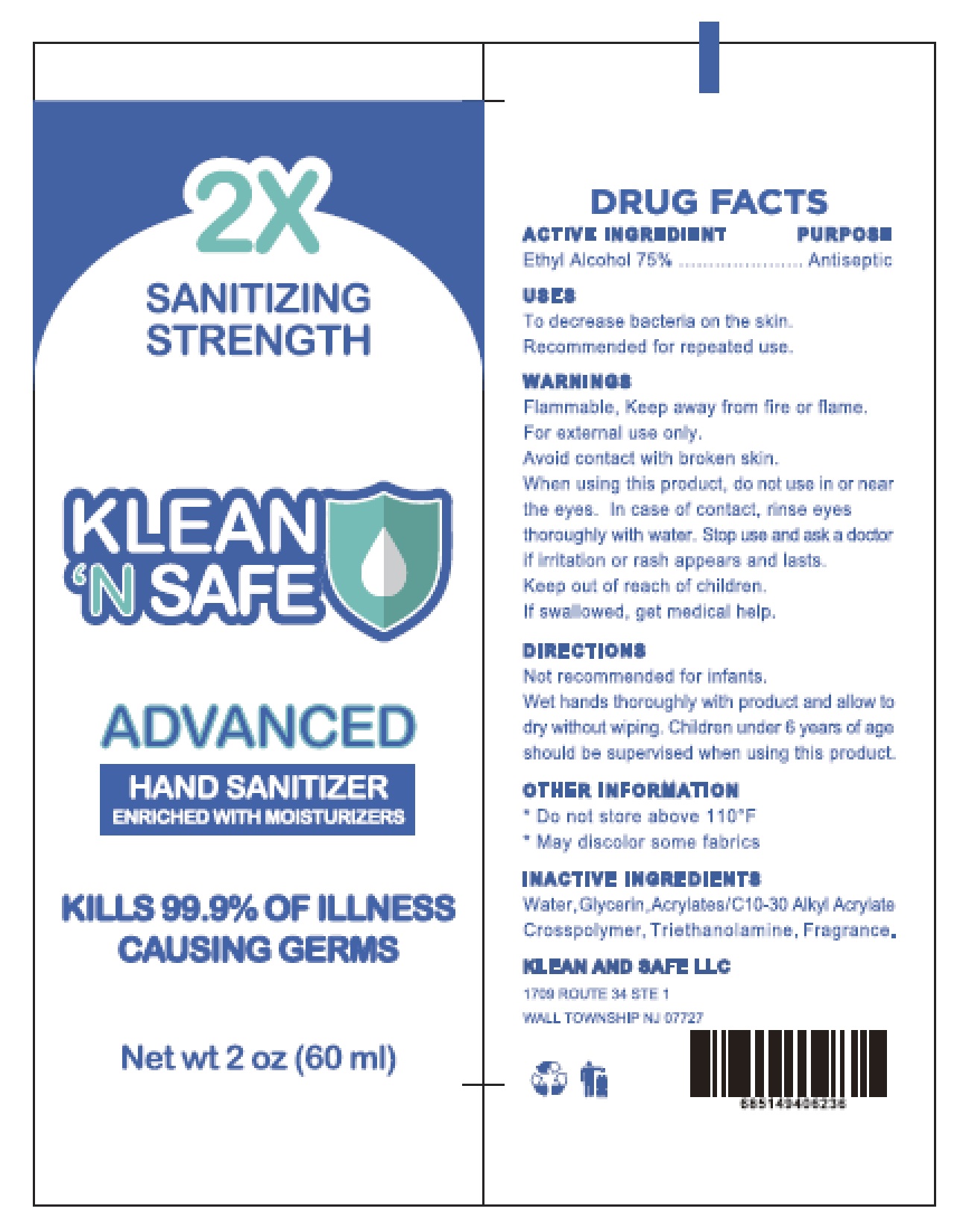 DRUG LABEL: Hand Sanitizer
NDC: 77616-012 | Form: GEL
Manufacturer: KLEAN AND SAFE LLC
Category: otc | Type: HUMAN OTC DRUG LABEL
Date: 20200521

ACTIVE INGREDIENTS: ALCOHOL 75 mL/100 mL
INACTIVE INGREDIENTS: WATER; GLYCERIN; CARBOMER INTERPOLYMER TYPE A (55000 CPS); TROLAMINE

Active Ingredient
Ethyl Alcohol 75%

Purpose
Antiseptic

Uses

To decrease bacteria on the skin.

Recommended for repeated use.

Warnings

Flammable. Keep away from fire or flame.

For external use only.

Avoid contact with broken skin.

When using this product, do not use in or near the eyes.In case of contact, rinse eyes thoroughly with

water.

Stop use and ask a doctor if irritation or rash appears and lasts.

Keep out of reach of children. If swallowed, get medical help.

Directions

Not recommended for infants.

Wet hands thoroughly with product and allow to dry without wiping.

Children under 6 years of age should be supervised when using this product.

Other Information

Do not store above 110°F. May discolor some fabrics.

Inactive Ingredients

Water,Glycerin, Acrylates/C1O-30 Alkyl Acrylate crosspolymer, Triethanoamine, Fragrance.